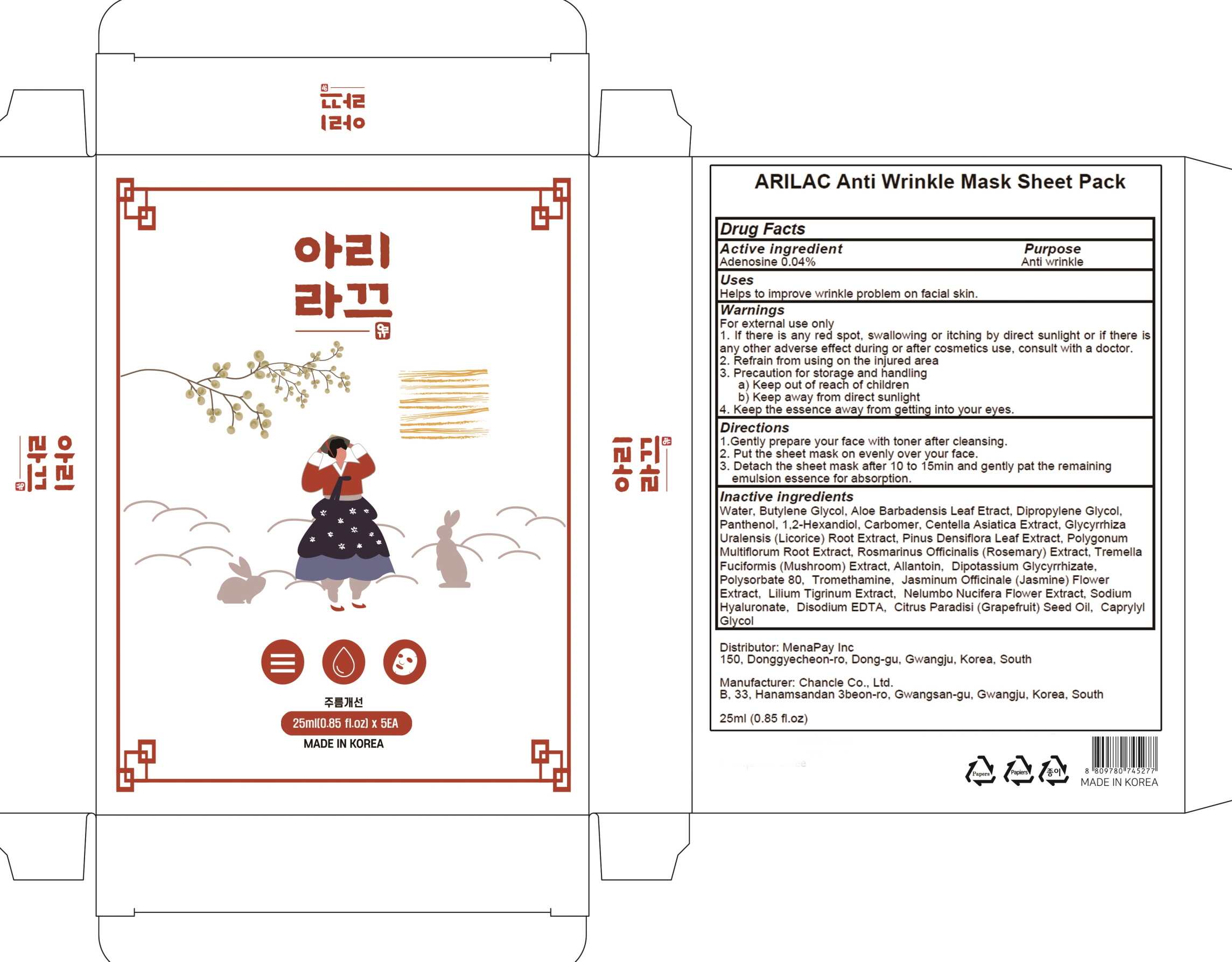 DRUG LABEL: ARILAC Anti Wrinkle Mask Sheet Pack
NDC: 81758-010 | Form: PATCH
Manufacturer: Menapay Inc.
Category: otc | Type: HUMAN OTC DRUG LABEL
Date: 20210513

ACTIVE INGREDIENTS: Adenosine 0.04 g/100 mL
INACTIVE INGREDIENTS: Water; Butylene Glycol

ACTIVE INGREDIENT

Adenosine 0.04%

INACTIVE INGREDIENTS

Water, Butylene Glycol, Aloe Barbadensis Leaf Etract, Dipropylene Glycol, Panthenol, 1,2-Hexandiol, Carbomer, Centella Asiatica Extract, Glycyrrhiza Uralensis (Licorice) Root Extract, Pinus Densiflora Leaf Extract, Polygonum Multiflorum Root Extract, Rosmarinus Officinalis (Rosemary) Extract, Tremella Fuciformis (Mushroom) Extract, Allantoin, Dipotassium Glycyrrhizate, Polysorbate 80, Tromethamine, Jasminum Officinale (Jasmine) Flower Extract, Lilium Tigrinum Extract, Nelumbo Nucifera Flower Extract, Sodium Hyaluronate, Disodium EDTA, Citrus Paradisi (Grapefruit) Seed Oil, Caprylyl Glycol

PURPOSE

Anti wrinkle

WARNINGS

For external use only
1. If there is any red spot, swallowing or itching by direct sunlight or if there is any other adverse effect during or after cosmetics use, consult with a doctor.
2. Refrain from using on the injured area
3. Precaution for storage and handling
a) Keep out of reach of children
b) Keep away from direct sunlight
4. Keep the essence away from getting into your eyes.

KEEP OUT OF REACH OF CHILDREN

Uses

Helps to improve wrinkle problem on facial skin.

Directions

1.Gently prepare your face with toner after cleansing.
2. Put the sheet mask on evenly over your face.
3. Detach the sheet mask after 10 to 15min and gently pat the remaining emulsion essence for absorption.